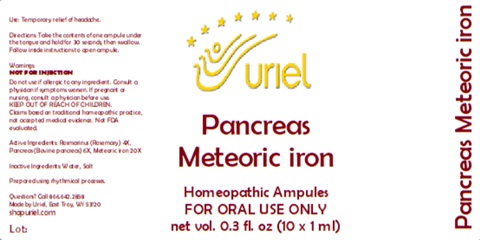 DRUG LABEL: Pancreas Meteoric Iron
NDC: 48951-8004 | Form: LIQUID
Manufacturer: Uriel Pharmacy Inc.
Category: homeopathic | Type: HUMAN OTC DRUG LABEL
Date: 20251114

ACTIVE INGREDIENTS: ROSMARINUS OFFICINALIS FLOWERING TOP 4 [hp_X]/1 mL; SUS SCROFA PANCREAS 6 [hp_X]/1 mL; IRON 20 [hp_X]/1 mL
INACTIVE INGREDIENTS: WATER; SODIUM CHLORIDE

Pancreas Meteoric Iron

PURPOSE

Use: Temporary relief of headache.

INDICATIONS AND USAGE

Directions: Take the contents of one ampule under the tongue and hold for 30 seconds, then swallow.
Follow inside instructions to open ampule.

DOSAGE AND ADMINISTRATION

FOR ORAL USE ONLY

Warnings:
NOT FOR INJECTION
Do not use if allergic to any ingredient. Consult a physician if symptoms worsen. If pregnant or nursing, consult a physician before use.
Claims based on traditional homeopathic practice, not accepted medical evidence. Not FDA evaluated.

KEEP OUT OF REACH OF CHILDREN.

ACTIVE INGREDIENT

Active Ingredients: Rosmarinus (Rosemary) 4X, Pancreas (Bovine pancreas) 6X, Meteoric iron 20X

Inactive Ingredients: Water, Salt

Prepared using rhythmical processes.

Questions? Call 866.642.2858
Made by Uriel, East Troy, WI 53120
shopuriel.com Lot: